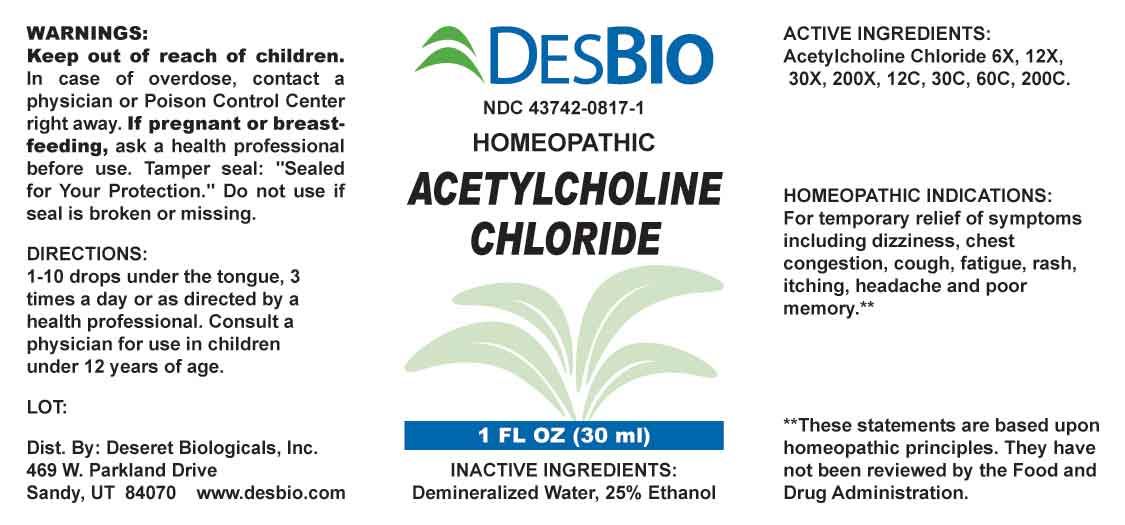 DRUG LABEL: Acetylcholine Chloride
NDC: 43742-0817 | Form: LIQUID
Manufacturer: Deseret Biologicals, Inc.
Category: homeopathic | Type: HUMAN OTC DRUG LABEL
Date: 20240305

ACTIVE INGREDIENTS: ACETYLCHOLINE CHLORIDE 6 [hp_X]/1 mL
INACTIVE INGREDIENTS: WATER; ALCOHOL

DRUG FACTS:

ACTIVE INGREDIENT:

Acetylcholine Chloride 6X, 12X, 30X, 200X, 12C, 30C, 60C, 200C.

PURPOSE:

For temporary relief of symptoms including dizziness, chest congestion, cough, fatigue, rash, itching, headache and poor memory.**

**These statements are based upon homeopathic principles. They have not been reviewed by the Food and Drug Administration.

WARNINGS:

Keep out of reach of children. In case of overdose, contact a physician or Poison Control Center right away.

If pregnant or breast-feeding, ask a health professional before use.

Tamper seal: "Sealed for Your Protection." Do not use if seal is broken or missing.

KEEP OUT OF REACH OF CHILDREN:

In case of overdose, contact a physician or Poison Control Center right away.

DIRECTIONS:

1-10 drops under the tongue, 3 times a day or as directed by a health professional. Consult a physician for use in children under 12 years of age.

INDICATIONS:

For temporary relief of symptoms including dizziness, chest congestion, cough, fatigue, rash, itching, headache and poor memory.**

**These statements are based upon homeopathic principles. They have not been reviewed by the Food and Drug Administration.

INACTIVE INGREDIENTS:

Demineralized Water, 25% Ethanol

QUESTIONS:

Dist. By: Deseret Biologicals, Inc.
469 W. Parkland Drive
Sandy, UT 84070 www.desbio.com

PACKAGE LABEL DISPLAY:

DESBIO

NDC 43742-0817-1

HOMEOPATHIC

ACETYLCHOLINE CHLORIDE

1 FL OZ (30 ml)